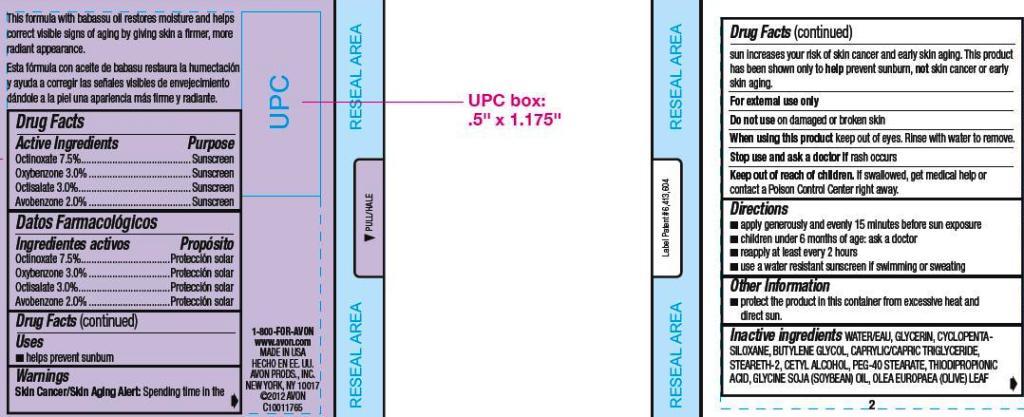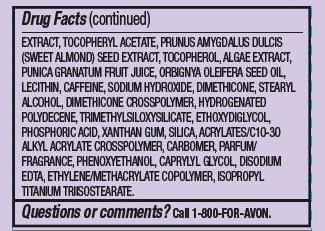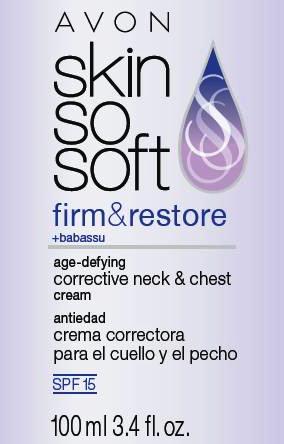 DRUG LABEL: Skin So Soft Firm and Restore
NDC: 10096-0153 | Form: CREAM
Manufacturer: Avon Products, Inc.
Category: otc | Type: HUMAN OTC DRUG LABEL
Date: 20120417

ACTIVE INGREDIENTS: OCTINOXATE	 7.5 mL/100 mL; OXYBENZONE	 3 mL/100 mL; OCTISALATE	 3 mL/100 mL; AVOBENZONE	 2 mL/100 mL

Drug Facts

Active Ingredients
Octinoxate 7.5%......................
Oxybenzone 3.0%...................
Octisalate 3.0%......................
Avobenzone 2.0% ..................

Purpose
................ Sunscreen
................ Sunscreen
................. Sunscreen
.................. Sunscreen

Uses
■ helps prevent sunburn

Warnings
Skin Cancer/Skin Aging Alert: Spending time in the sun increases your risk of skin cancer and early skin aging. This product
has been shown only to help prevent sunburn, not skin cancer or early skin aging.

For external use only

Do not use on damaged or broken skin

When using this product keep out of eyes. Rinse with water to remove.

Stop use and ask a doctor if rash occurs

Keep out of reach of children. If swallowed, get medical help or
contact a Poison Control Center right away.

Directions
■ apply generously and evenly 15 minutes before sun exposure
■ children under 6 months of age: ask a doctor
■ reapply at least every 2 hours
■ use a water resistant sunscreen if swimming or sweating

Other Information
■ protect the product in this container from excessive heat and
direct sun.

INACTIVE INGREDIENT

Inactive ingredients WATER/EAU, GLYCERIN, CYCLOPENTASILOXANE, BUTYLENE GLYCOL, CAPRYLIC/CAPRIC TRIGLYCERIDE, STEARETH-2, CETYL ALCOHOL, PEG-40 STEARATE, THIODIPROPIONIC ACID, GLYCINE SOJA (SOYBEAN) OIL, OLEA EUROPAEA (OLIVE) LEAFEXTRACT, TOCOPHERYL ACETATE, PRUNUS AMYGDALUS DULCIS (SWEET ALMOND) SEED EXTRACT, TOCOPHEROL, ALGAE EXTRACT, PUNICA GRANATUM FRUIT JUICE, ORBIGNYA OLEIFERA SEED OIL, LECITHIN, CAFFEINE, SODIUM HYDROXIDE, DIMETHICONE, STEARYL ALCOHOL, DIMETHICONE CROSSPOLYMER, HYDROGENATED POLYDECENE, TRIMETHYLSILOXYSILICATE, ETHOXYDIGLYCOL, PHOSPHORIC ACID, XANTHAN GUM, SILICA, ACRYLATES/C10-30 ALKYL ACRYLATE CROSSPOLYMER, CARBOMER, PARFUM/ FRAGRANCE, PHENOXYETHANOL, CAPRYLYL GLYCOL, DISODIUM EDTA, ETHYLENE/METHACRYLATE COPOLYMER, ISOPROPYL TITANIUM TRIISOSTEARATE.

Questions or comments? Call 1-800-FOR-AVON.